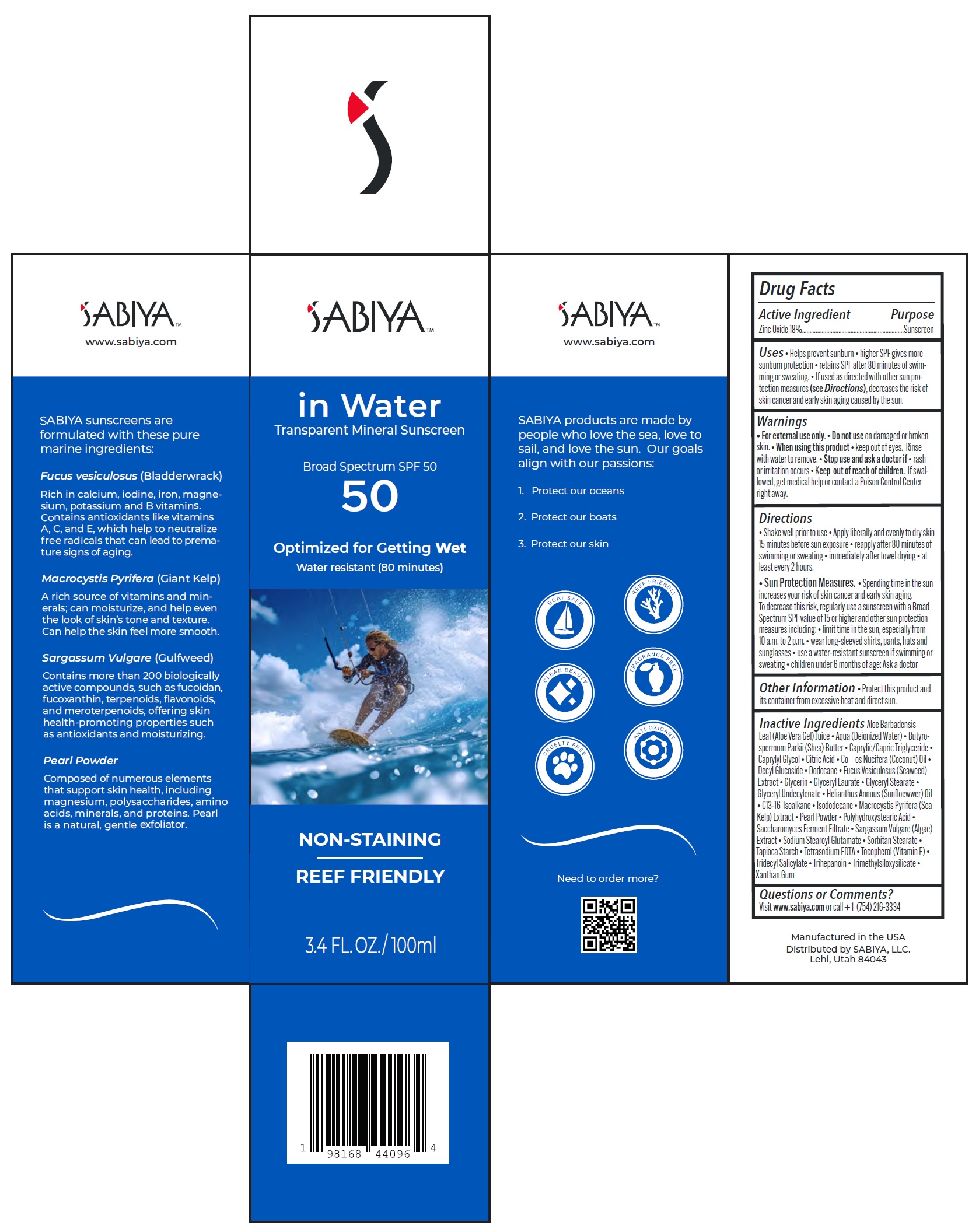 DRUG LABEL: SABIYA Broad Spectrum SPF-50
NDC: 84307-486 | Form: CREAM
Manufacturer: SABIYA, LLC
Category: otc | Type: HUMAN OTC DRUG LABEL
Date: 20240509

ACTIVE INGREDIENTS: ZINC OXIDE 180 mg/1 mL
INACTIVE INGREDIENTS: ALOE VERA LEAF; WATER; SHEA BUTTER; MEDIUM-CHAIN TRIGLYCERIDES; CAPRYLYL GLYCOL; CITRIC ACID MONOHYDRATE; COCONUT OIL; DECYL GLUCOSIDE; DODECANE; GLYCERIN; GLYCERYL LAURATE; GLYCERYL MONOSTEARATE; ISODODECANE; PEARL (HYRIOPSIS CUMINGII); SODIUM STEAROYL GLUTAMATE; SORBITAN MONOSTEARATE; STARCH, TAPIOCA; EDETATE SODIUM; .ALPHA.-TOCOPHEROL; TRIDECYL SALICYLATE; XANTHAN GUM

SABIYA Broad Spectrum SPF-50

Active Ingredient

Zinc Oxide 18%

Purpose

Sunscreen

Uses

- Helps prevent sunburn
- higher SPF gives more sunburn protection
- retains SPF after 80 minutes of swimming or sweating.
- If used as directed with other sun protection measures (see Directions), decreases the risk of skin cancer and early skin aging caused by the sun.

Warnings

- For external use only.

Do not use

- on damaged or broken skin.

When using this product

- keep out of eyes. Rinse with water to remove.

Stop use and ask a doctor if

- rash or irritation occurs

Keep out of reach of children.

- If swallowed, get medical help or contact a Poison Control Center right away.

Directions

- Shake well prior to use
- Apply liberally and evenly to dry skin 15 minutes before sun exposure
- reapply after 80 minutes of swimming or sweating
- immediately after towel drying
- at least every 2 hours.
- Sun Protection Measures.
- Spending time in the sun increases your risk of skin cancer and early skin aging. To decrease this risk, regularly use a sunscreen with a Broad Spectrum SPF value of 15 or higher and other sun protection measures including:
- limit time in the sun, especially from 10 a.m. to 2 p.m.
- wear long-sleeved shirts, pants, hats and sunglasses
- use a water-resistant sunscreen if swimming or sweating
- children under 6 months of age: Ask a doctor

Other Information

- Protect this product and its container from excessive heat and direct sun.

Inactive Ingredients

Aloe Barbadensis Leaf (Aloe Vera Gel) Juice • Aqua (Deionized Water) • Butyrospermum Parkii (Shea) Butter • Caprylic/Capric Triglyceride • Caprylyl Glycol • Citric Acid • Coos Nucifera (Coconut) Oil • Decyl Glucoside • Dodecane • Fucus Vesiculosus (Seaweed) Extract • Glycerin• Glyceryl Laurate • Glyceryl Stearate • Glyceryl Undecylenate • Isododecane • Macrocystis Pyrifera (Sea Kelp) Extract • Parfum (Fragrance) • Pearl Powder • Polyhydroxystearic Acid •Saccharomyces Ferment Filtrate • Sargassum Vulgare (Algae) Extract • Sodium Stearoyl Glutamate • Sorbitan Stearate •Tapioca Starch • Tetrasodium EDTA • Tocopherol (Vitamin E) • Tridecyl Salicylate • Trimethylsiloxysilicate • Xanthan Gum •

Questions or Comments?

Visit www.sabiya.comor call + 1 (754) 216-3334